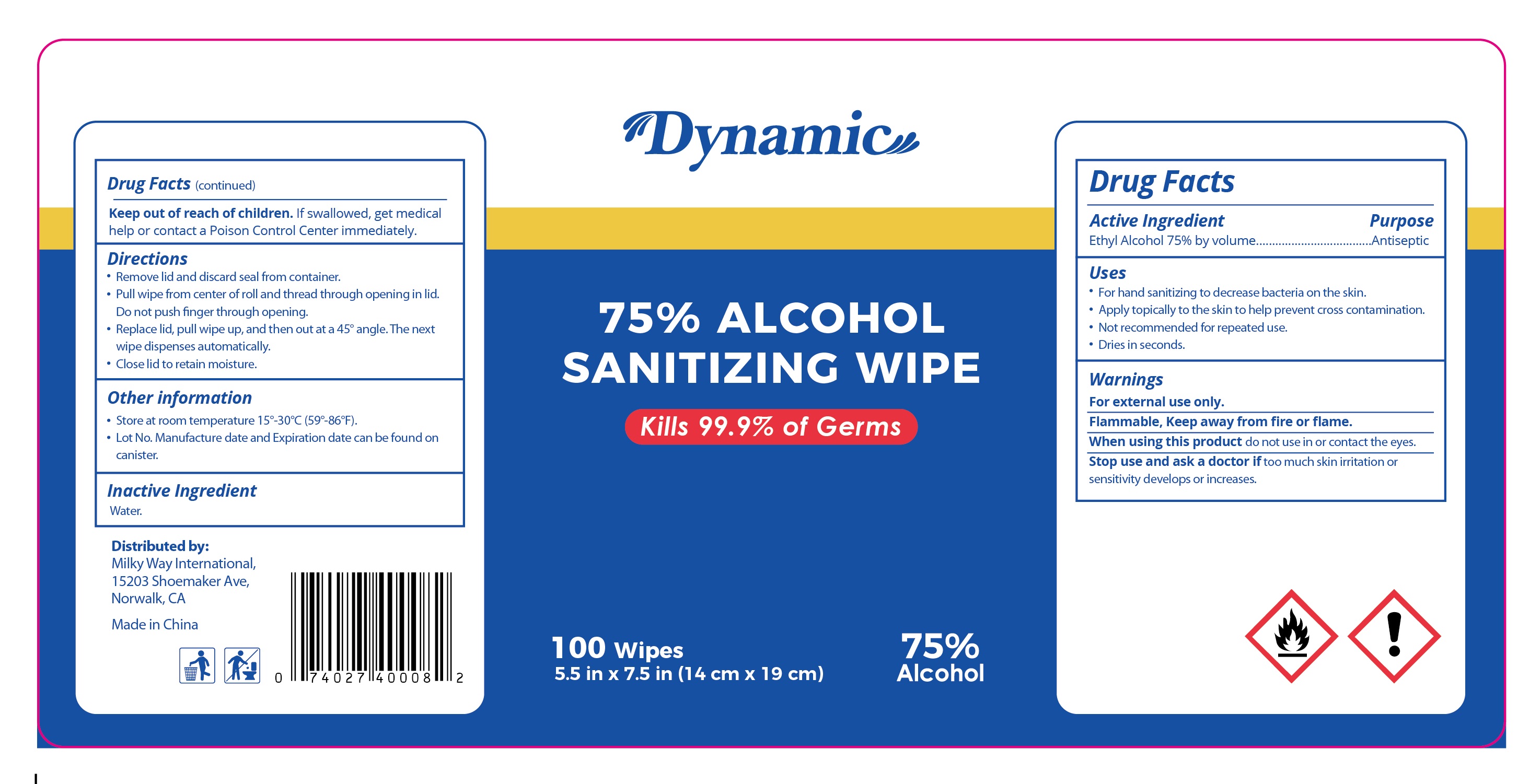 DRUG LABEL: Dynamic Sanitizing Alcohol wipes
NDC: 79203-002 | Form: CLOTH
Manufacturer: Milky Way International Trading Corp
Category: otc | Type: HUMAN OTC DRUG LABEL
Date: 20220208

ACTIVE INGREDIENTS: ALCOHOL 75 mL/100 mL
INACTIVE INGREDIENTS: WATER

79203-002 Dynamic Sanitizing Alcohol wipes 75% alcohol

Active Ingredient

Ethyl Alcohol 75% by volume

Purpose

Antiseptic

USE

●For hand sanitizing to decrease bacteria on the skin.
●Apply topically to the skin to help prevent cross contamination.
●Not recommended for repeated use.
●Dries in seconds.

Warning

For external use only.
Flammable, Keep away from fire or flame.
When using this product do not use in or contact the eyes.
Stop use and ask a doctor if too much skin irritation or
sensitivity develops or increases.

keep out of reach of children. If swallowed, contact medical help or call Poison Control immediately.

Directions

Remove lid and discard seal from container.
.Pull wipe from center of roll and thread through opening in lid.
Do not push finger through opening.
Replace lid, pull wipe up, and then out at a 45° angle. The next
wipe dispenses automatically.
.Close lid to retain moisture.
other information
.Store at room temperature 15°-30℃(59-86F).
. Lot No.Manufacture date and Expiration date can be found on
canister.

Inactive ingredients

Water